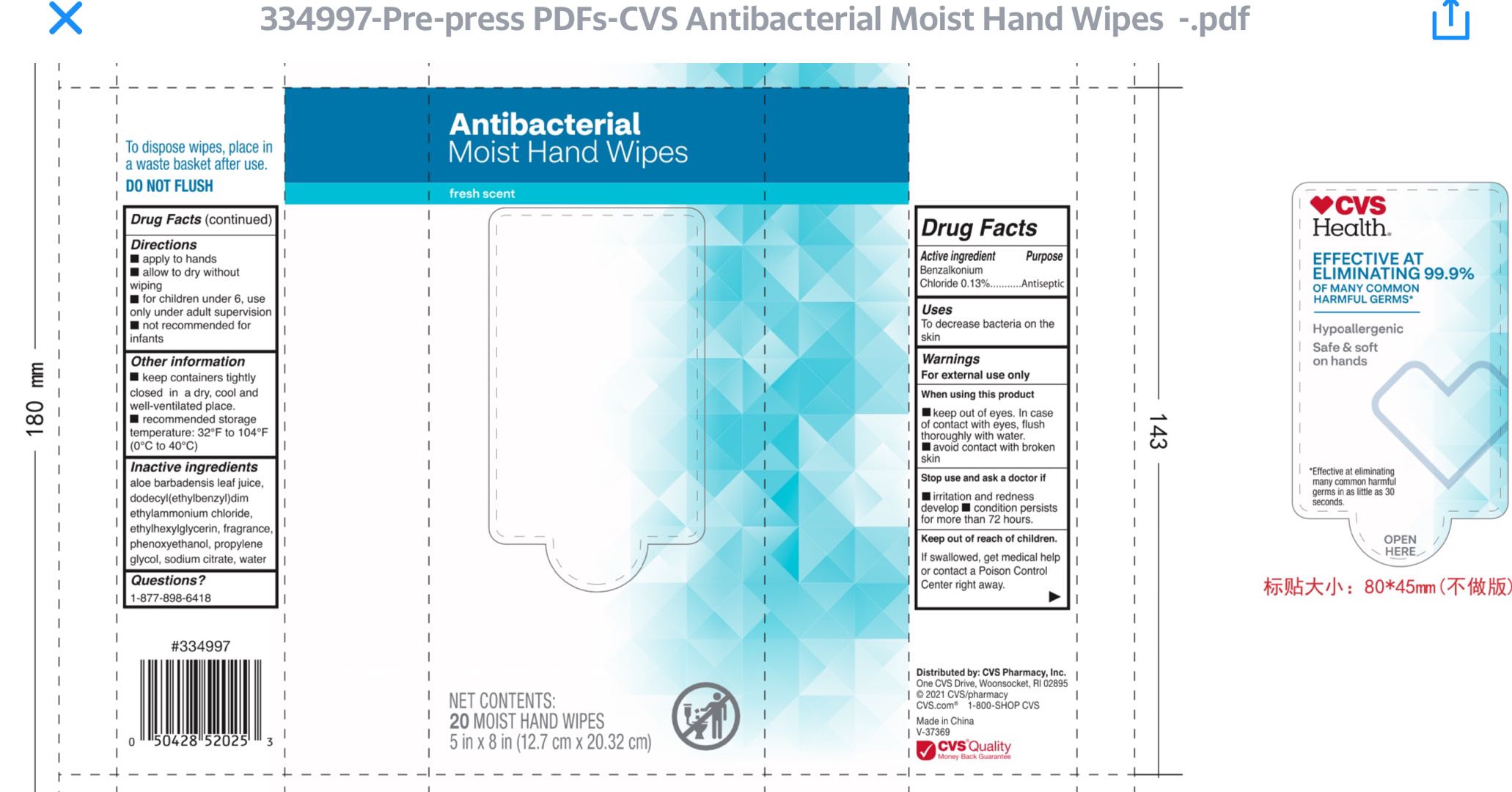 DRUG LABEL: CVS Health Antibacterial Moist Hand Wipes
NDC: 51316-001 | Form: SOLUTION
Manufacturer: CVS PHARMACY, INC
Category: otc | Type: HUMAN OTC DRUG LABEL
Date: 20210527

ACTIVE INGREDIENTS: BENZALKONIUM CHLORIDE 0.13 g/100 g
INACTIVE INGREDIENTS: WATER; ALOE VERA LEAF; ETHYLHEXYLGLYCERIN; PROPYLENE GLYCOL; PHENOXYETHANOL; SODIUM CITRATE

51316-001 CVS SKU 334997

Active Ingredient

Benzalkonium Chloride 0.13%

Purpose

Antiseptic

Use

To decrease bacteria on the skin

Warnings

For external use only

- When using this product keep out of eyes. In case of contact with eyes, flush thoroughly with water.
- Avoid contact with broken skin

Stop use and ask a doctor if irritation and redness develop, condition persists for more than 72 hours

Keep out of reach of children. If swallowed, get medical help or contact a Poison Control Center right away.

Directions

- Apply to hands
- Allow to dry without wiping
- For children under 6, use only under adult supervision
- Not recommended for infants

Other information

- Keep containers tightly closed in a dry, cool and well ventilated place
- Recommended storage temperature: 32F to 104F (0C to 40C)

Inactive ingredients

Aloe Barbadensis Leaf Juice, Dodecyl (ethylbenzyl) Dimethylammonium Chloride, Ethylhexylglycerin, Fragrance, Phenoxyethanol, Propylene Glycol, Sodium Citrate, Water